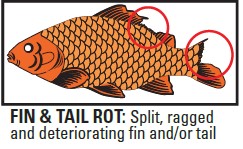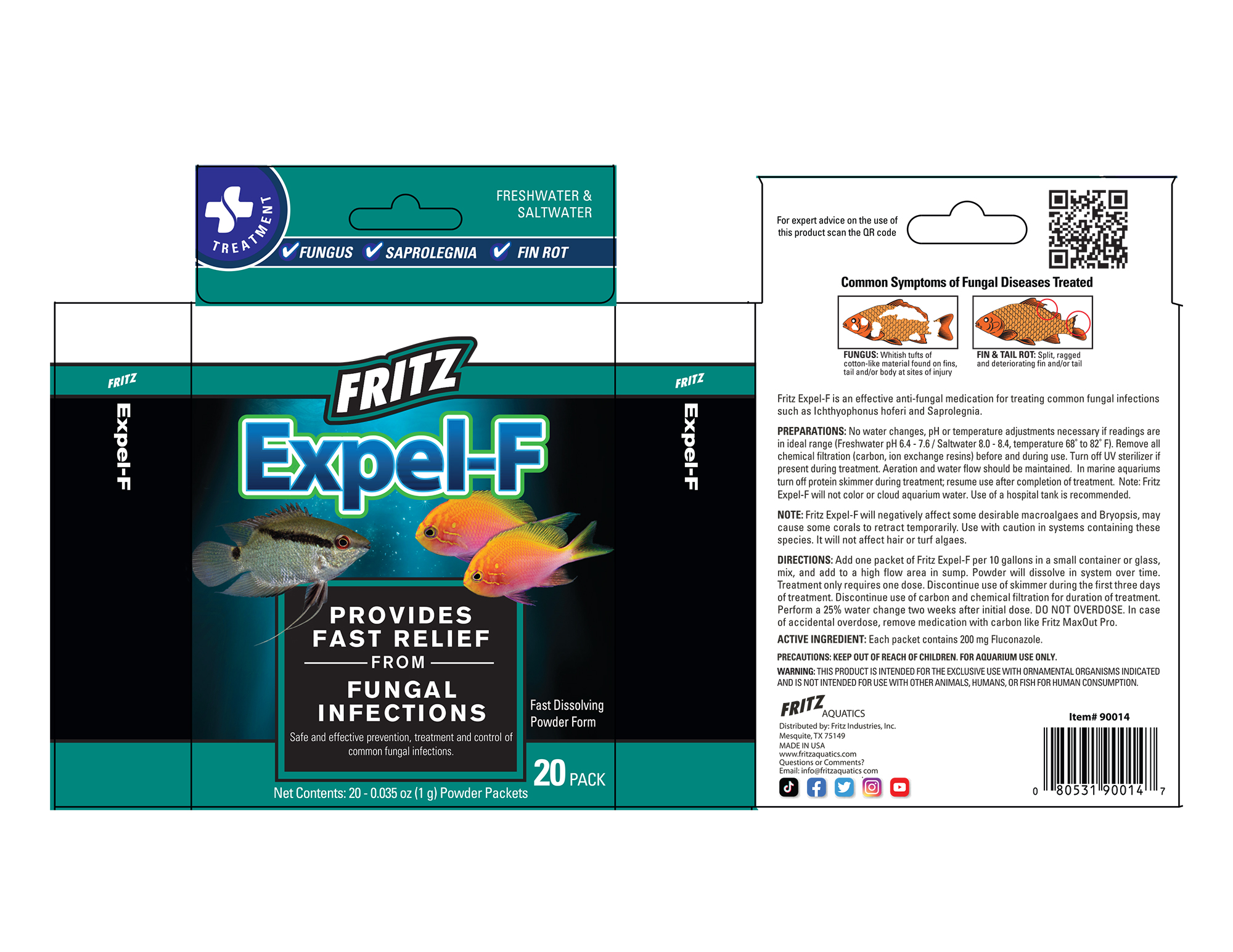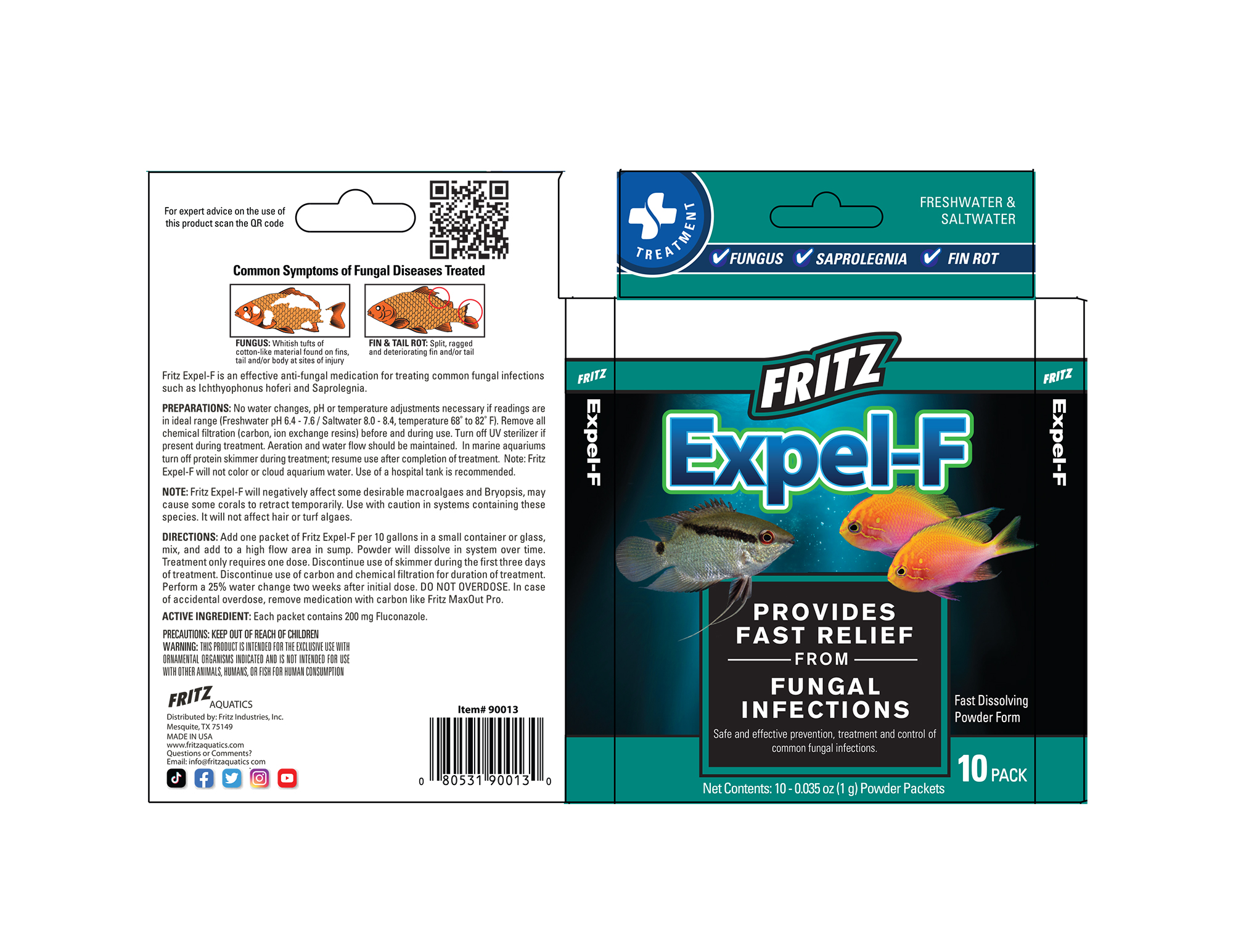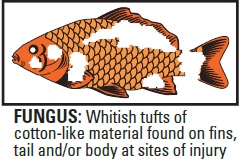 DRUG LABEL: Expel-F
NDC: 53745-015 | Form: POWDER
Manufacturer: Fritz Industries
Category: animal | Type: OTC ANIMAL DRUG LABEL
Date: 20211210

ACTIVE INGREDIENTS: FLUCONAZOLE 200 mg/1 g
INACTIVE INGREDIENTS: DEXTROSE, UNSPECIFIED FORM; SILICON DIOXIDE

Expel-F

Indications:

Common Symptoms of Fungal Diseases Treated

FUNGUS: Whitish tufts of cotton-like material found on fins, tail and/or body at sites of injury

FIN & TAIL ROT: Split, ragged and deteriorating fin and/or tail

Fritz Expel-F is an effective anti-fungal medication for treating common fungal infections such as Ichthyophonus hoferi and Saprolegnia.

PREPARATIONS:

No water changes, pH or temperature adjustments necessary if readings are in ideal range (Freshwater pH 6.4 - 7.6 / Saltwater 8.0 - 8.4, temperature 68° to 82° F). Remove all chemical filtration (carbon, ion exchange resins) before and during use. Turn off UV sterilizer if present during treatment. Aeration and water flow should be maintained. In marine aquariums turn off protein skimmer during treatment; resume use after completion of treatment. Note: Fritz Expel-F will not color or cloud aquarium water. Use of a hospital tank is recommended.

NOTE:

Fritz Expel-F will negatively affect some desirable macroalgaes and Bryopsis, may cause some corals to retract temporarily. Use with caution in systems containing these species. It will not affect hair or turf algaes.

DIRECTIONS:

Add one packet of Fritz Expel-F per 10 gallons in a small container or glass, mix, and add to a high flow area in sump. Powder will dissolve in system over time. Treatment only requires one dose. Discontinue use of skimmer during the first three days of treatment. Discontinue use of carbon and chemical filtration for duration of treatment. Perform a 25% water change two weeks after initial dose. DO NOT OVERDOSE. In case
of accidental overdose, remove medication with carbon like Fritz MaxOut Pro.

ACTIVE INGREDIENT:

Each packet contains 200 mg Fluconazole.

KEEP OUT OF REACH OF CHILDREN

WARNINGS

THIS PRODUCT IS INTENDED FOR THE EXCLUSIVE USE WITH ORNAMENTAL ORGANISMS INDICATED AND IS NOT INTENDED FOR USE WITH OTHER ANIMALS, HUMANS, OR FISH FOR HUMAN CONSUMPTION

FRITZ

Expel-F

Provides Fast Relief from Fungal Infections

Safe and effective prevention, treatment and control of common fungal infections.

Fast Dissolving Powder Form

Net Contents: 10-0.035 oz (1g) Powder Packets

FRITZ AQUATICS

Distributed by: Fritz Industries, Inc.

Mesquite, TX 75149

MADE IN USA

www.fritzaquatics.com

Questions or Comments?

Email: info@fritzaquatics.com